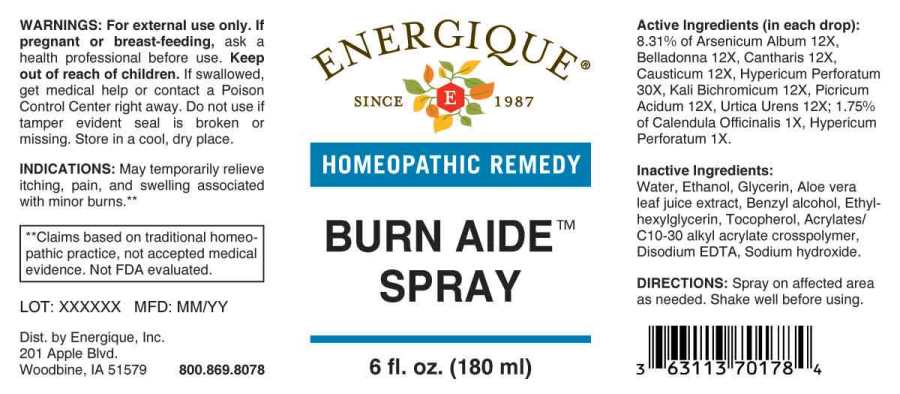 DRUG LABEL: Burn Aide
NDC: 44911-0662 | Form: SPRAY
Manufacturer: Energique, Inc.
Category: homeopathic | Type: HUMAN OTC DRUG LABEL
Date: 20240805

ACTIVE INGREDIENTS: CALENDULA OFFICINALIS FLOWERING TOP 1 [hp_X]/1 mL; HYPERICUM PERFORATUM WHOLE 1 [hp_X]/1 mL; ARSENIC TRIOXIDE 12 [hp_X]/1 mL; ATROPA BELLADONNA 12 [hp_X]/1 mL; LYTTA VESICATORIA 12 [hp_X]/1 mL; CAUSTICUM 12 [hp_X]/1 mL; POTASSIUM DICHROMATE 12 [hp_X]/1 mL; PICRIC ACID 12 [hp_X]/1 mL; URTICA URENS WHOLE 12 [hp_X]/1 mL
INACTIVE INGREDIENTS: GLYCERIN; WATER; ALOE VERA LEAF; BENZYL ALCOHOL; ETHYLHEXYLGLYCERIN; TOCOPHEROL; CARBOMER COPOLYMER TYPE A (ALLYL PENTAERYTHRITOL CROSSLINKED); EDETATE DISODIUM ANHYDROUS; SODIUM HYDROXIDE; ALCOHOL

DRUG FACTS:

ACTIVE INGREDIENTS:

(in each drop): 8.31% of Arsenicum Album 12X, Belladonna 12X, Cantharis 12X, Causticum 12X, Hypericum Perforatum 30X, Kali Bichromicum 12X, Picricum Acidum 12X, Urtica Urens 12X; 1.75% of Calendula Officinalis 1X, Hypericum Perforatum 1X.

PURPOSE:

May temporarily relieve itching, pain, and swelling associated with minor burns.**

**Claims based on traditional homeopathic practice, not accepted medical evidence. Not FDA evaluated.

USES:

May temporarily relieve itching, pain, and swelling associated with minor burns.**

**Claims based on traditional homeopathic practice, not accepted medical evidence. Not FDA evaluated.

WARNINGS:

For external use only.

If pregnant or breast-feeding, ask a health professional before use.

Keep out of reach of children. If swallowed, get medical help or contact a Poison Control Center right away.

Do not use if tamper evident seal is broken or missing. Store in a cool, dry place.

Keep out of reach of children. If swallowed, get medical help or contact a Poison Control Center right away.

DIRECTIONS:

Spray on affected area as needed. Shake well before using.

INACTIVE INGREDIENTS:

Water, Ethanol, Glycerin, Aloe vers leaf juice extract, Benzyl alcohol, Ethylhexylglycerin, Tocopherol, Acrylates/C10-30 alkyl acrylate crosspolymer, Disodium EDTA, Sodium hydroxide.

QUESTIONS:

Dist. by Energique, Inc.

201 Apple Blvd

Woodbine, IA 51579 800-869-8078

PACKAGE LABEL DISPLAY:

ENERGIQUE

SINCE 1987

HOMEOPATHIC REMEDY

BURN AIDE

SPRAY

6 fl. OZ. (180 ml)